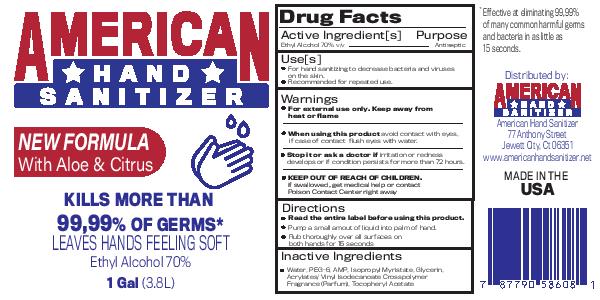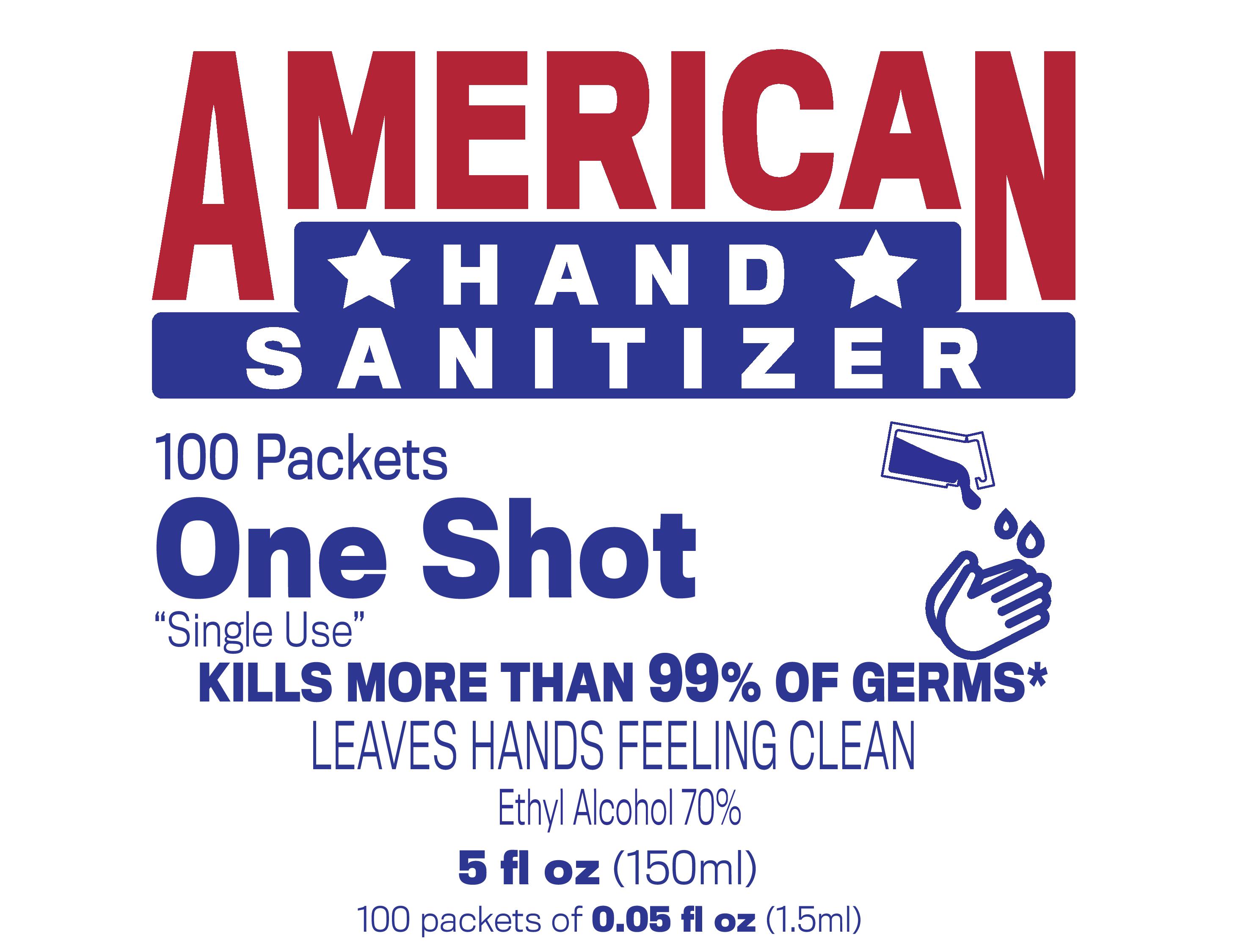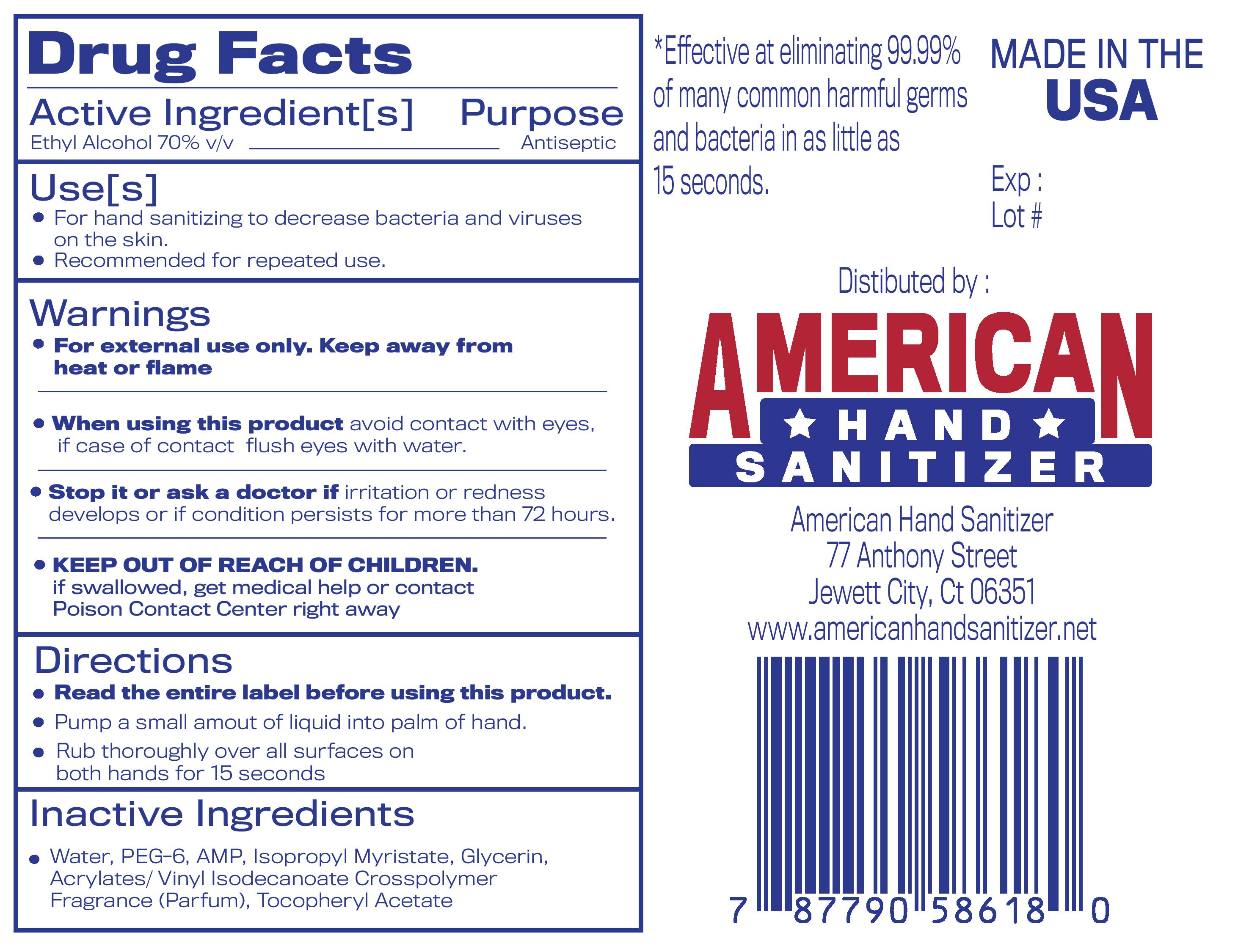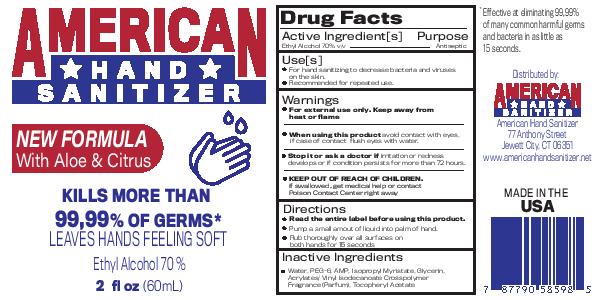 DRUG LABEL: American Hand Sanitizer
NDC: 79421-004 | Form: GEL
Manufacturer: American Hand Sanitizer LLC
Category: otc | Type: HUMAN OTC DRUG LABEL
Date: 20200813

ACTIVE INGREDIENTS: ALCOHOL 70 mL/100 mL
INACTIVE INGREDIENTS: GLYCERIN; HYDROGEN PEROXIDE; WATER

American Hand Sanitizer Gel 70

Active Ingredient(s)

Ethyl Alcohol 80% v/v

Purpose

Antiseptic

Use

For hand sanitizer to decrease bacteria and viruses on the skin.

Recommended for repeated use.

Warnings

For external use only. Flammable. Keep away from heat or flame

Do not use

- in children less than 2 months of age
- on open skin wounds

When using this product avoid contact with eyes. In case of contact with flush eyes with water.

Stop use and ask a doctor if irritation or redness develops or if condition persists for more than 72 hours.

Keep out of reach of children. If swallowed, get medical help or contact a Poison Control Center right away.

Directions

- Read the entire label before using this product.
- Pump a small amout of liquid into palm of hand.
- Rub thoroughly over all surfaces on both hands for 15 seconds

Other information

- Store between 15-30C (59-86F)
- Avoid freezing and excessive heat above 40C (104F)

Inactive ingredients

glycerin, hydrogen peroxide, water